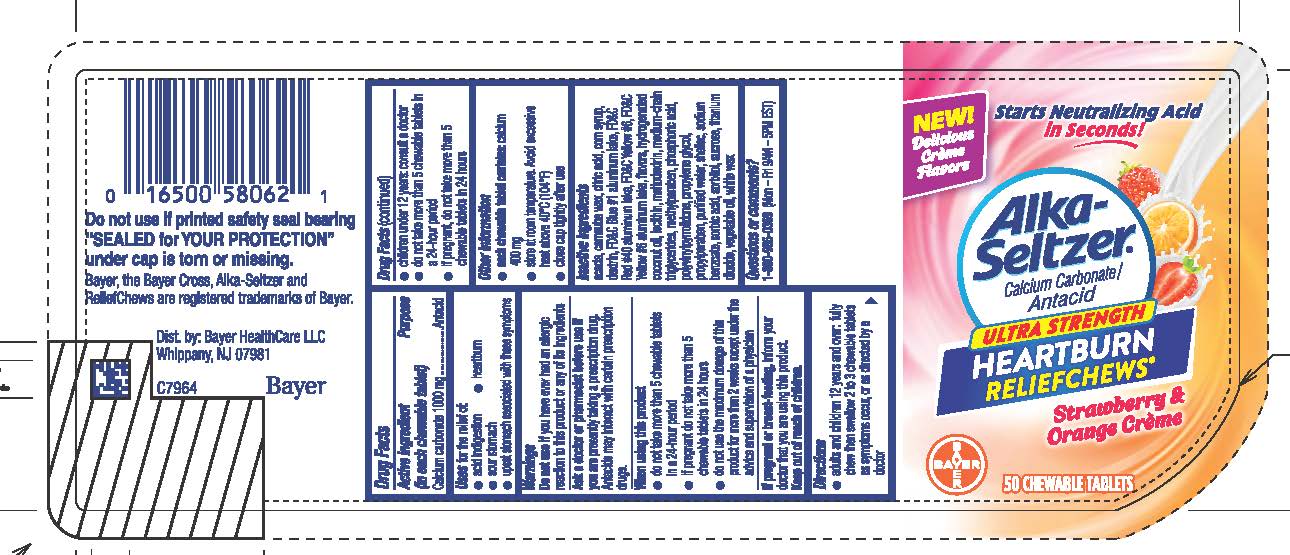 DRUG LABEL: Alka-Seltzer Ultra Strength Heartburn ReliefChews
NDC: 0280-0059 | Form: TABLET, CHEWABLE
Manufacturer: Bayer HealthCare LLC.
Category: otc | Type: HUMAN OTC DRUG LABEL
Date: 20251204

ACTIVE INGREDIENTS: CALCIUM CARBONATE 1000 mg/1 1
INACTIVE INGREDIENTS: ACACIA; CORN SYRUP; FD&C YELLOW NO. 6; MALTODEXTRIN; METHYLPARABEN; SHELLAC; SORBIC ACID; WHITE WAX; TITANIUM DIOXIDE; HYDROGENATED COCONUT OIL; WATER; SODIUM BENZOATE; SUCROSE; CARNAUBA WAX; FD&C BLUE NO. 1--ALUMINUM LAKE; MEDIUM-CHAIN TRIGLYCERIDES; PROPYLPARABEN; PHOSPHORIC ACID; PROPYLENE GLYCOL; SORBITOL

Alka-Seltzer Ultra Strength Heartburn ReliefChews Strawberry & Orange Creme UI 1614243 & 1614244

Drug Facts

Active ingredient (in each chewable tablet)

Calcium carbonate 1000 mg

Purpose

Antacid

Uses

Uses for the relief of:

● acid indigestion ● heartburn ● sour stomach

● upset stomach associated with these symptoms

Warnings
Do not use if you have ever had an allergic reaction to this product or any of its ingredients

Ask a doctor or pharmacist before use if you are presently taking a prescription drug. Antacids may interact with certain prescription drugs.

When using this product
● do not take more than 5 chewable tablets in a 24-hour
period

● if pregnant do not take more than 5 chewable tablets in 24

hours

● do not use the maximum dosage of this product for more

than 2 weeks except under the advice and supervision of a

physician

PREGNANCY OR BREAST FEEDING

If pregnant or breast-feeding, inform your doctor that you are using this product.

Keep out of reach of children.

Directions

● adults and children 12 years and over: fully chew then swallow 2 to 3 chewable tablets as symptoms occur, or as directed by a doctor

● children under 12 years: consult a doctor

● do not take more than 5 chewable tablets in a 24-hour period

● if pregnant, do not take more than 5 chewable tablets in 24

hours

Other information

● each chewable tablet contains: calcium 400 mg

● store at room temperature. Avoid excessive heat above 40°C

(104°F).

● close cap tightly after use

INACTIVE INGREDIENT

Inactive ingredients acacia, carnauba wax, citric acid, corn syrup, dextrin, FD&C Blue #1 aluminum lake, FD&C Red #40 aluminum lake, FD&C Yellow #6, FD&C Yellow #6 aluminum lake, flavors, hydrogenated coconut oil, lecithin, maltodextrin, medium-chain triglycerides, methylparaben, phosphoric acid, polyvinylpyrrolidone, propylene glycol, propylparaben, purified water, shellac, sodium benzoate, sorbic acid, sorbitol, sucrose, titanium dioxide, vegetable oil, white wax

Questions or comments? 1-800-986-0369

(Mon – Fri 9AM – 5PM EST)

50 Tablet bottle label

NEW!

Delicious

Creme

Flavors

Starts Neutralizing Acid

in Seconds!

Alka-Seltzer®

Calcium Carbonate/Antacid

ULTRA STRENGTH

HEARTBURN

RELIEFCHEWS®

Strawberry &

Orange Creme

50 CHEWABLE TABELTS